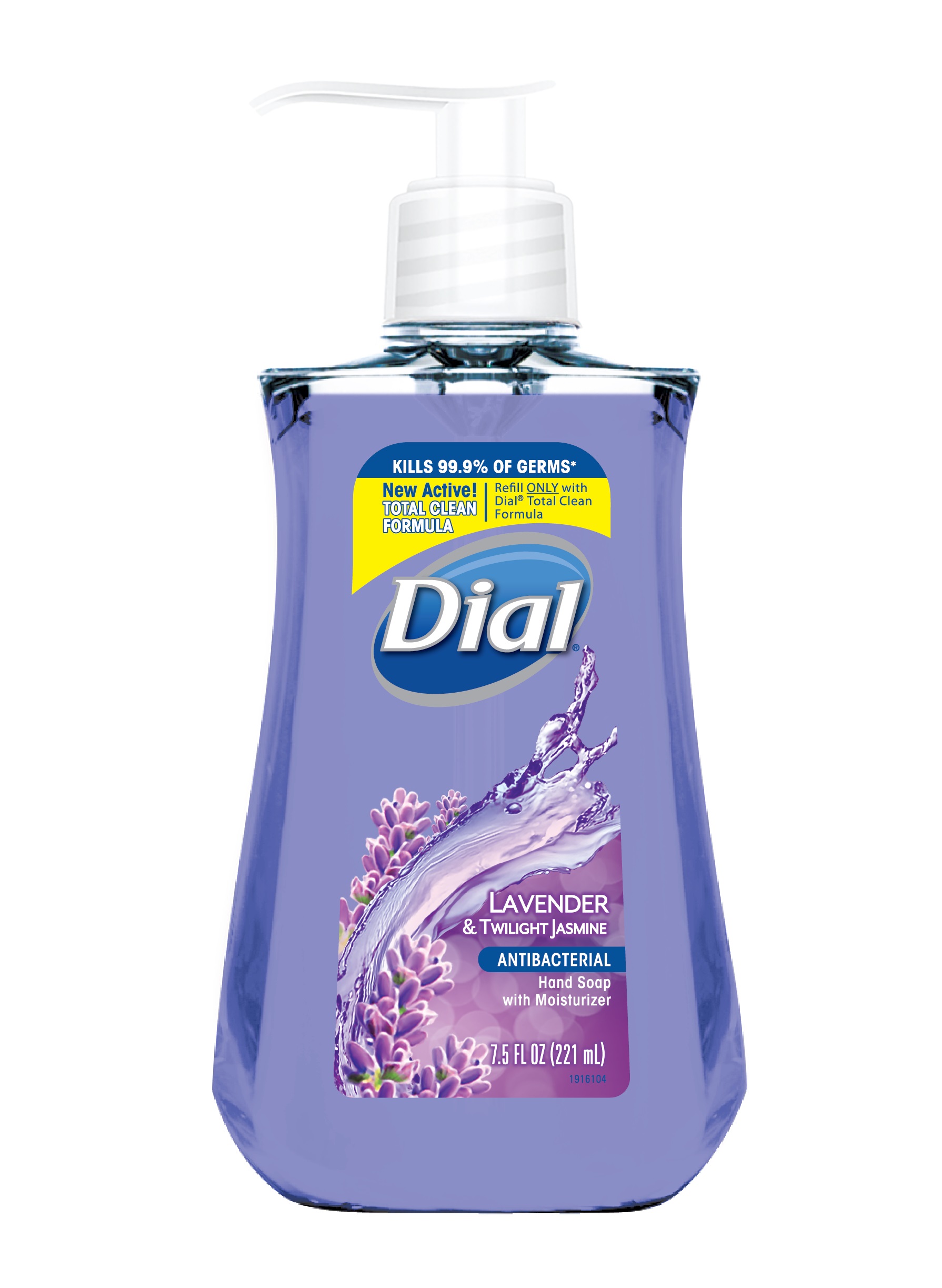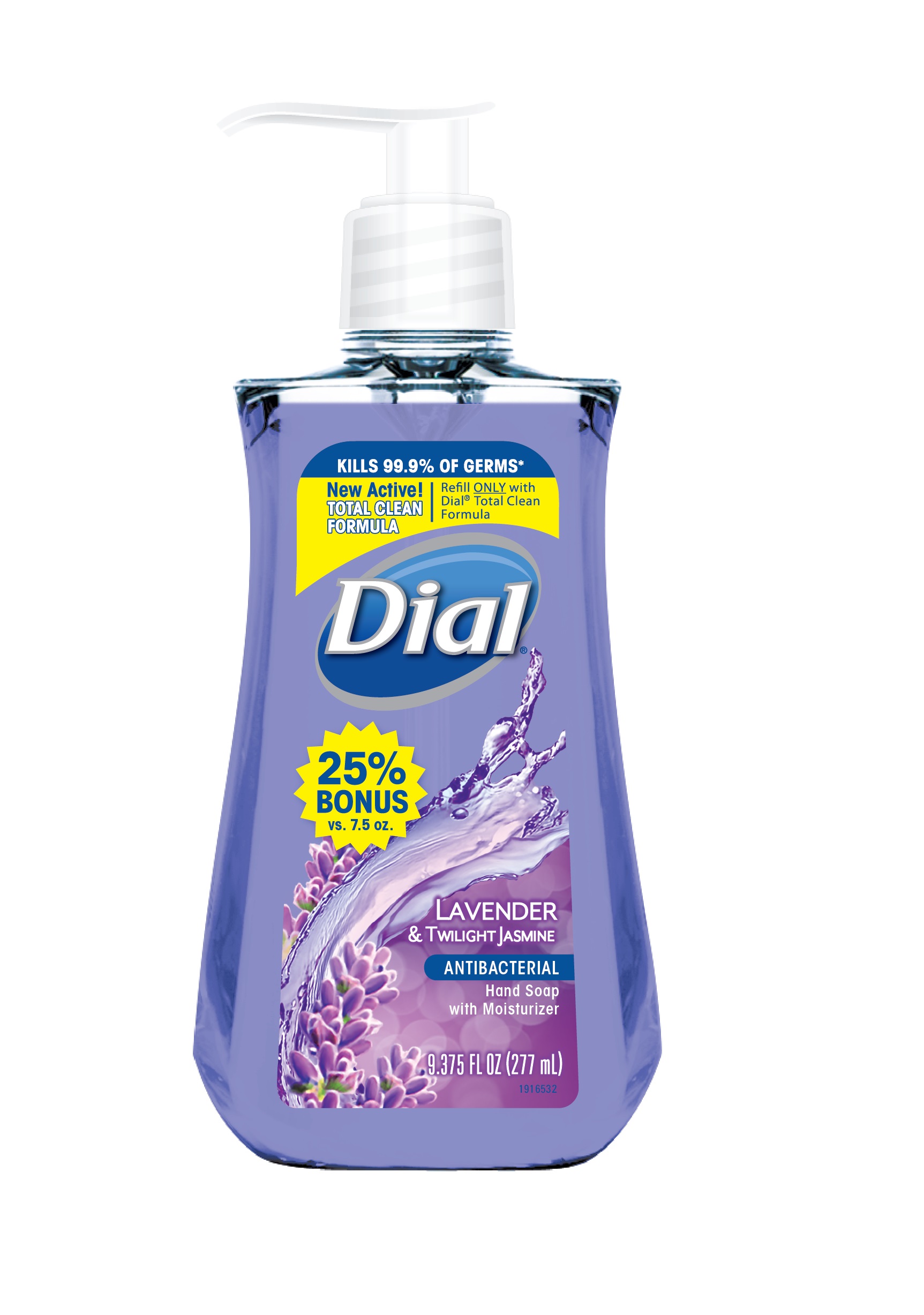 DRUG LABEL: Benzethonium Chloride Solution
NDC: 54340-254 | Form: SOLUTION
Manufacturer: The Dial Corporation, A Henkel Company
Category: otc | Type: HUMAN OTC DRUG LABEL
Date: 20150107

ACTIVE INGREDIENTS: BENZETHONIUM CHLORIDE .1 g/100 mL
INACTIVE INGREDIENTS: D&C RED NO. 33; LAURAMINE OXIDE; LAURAMIDOPROPYLAMINE OXIDE; COCO MONOETHANOLAMIDE; PEG-120 METHYL GLUCOSE DIOLEATE; GLYCERIN; CETRIMONIUM CHLORIDE; EDETATE SODIUM; SODIUM BENZOATE; CITRIC ACID MONOHYDRATE; FD&C BLUE NO. 1

Dial Lavender & Twilight Jasmine Antibacterial Hand Soap with Moisturizer

Drug Facts

ACTIVE INGREDIENT

Benzethonium Chloride 0.10%

PURPOSE

Antibacterial

PURPOSE

Uses - For handwashing to decrease bacteria on the skin

WARNINGS

For external use only

When using this product - Avoid contact with eyes. In case of eye contact, flush with water.

Stop use and ask a doctor if irritation and redness develops.

Keep out of reach of children. If swallowed, get medical help or contact a Poison Control Center right away.

Directions

- pump into hands, wet as needed
- lather vigorously for at least 15 seconds
- wash skin, rinse thoroughly and dry

INACTIVE INGREDIENT

Inactive Ingredients: Water, Centrimonium Chloride, Glycerin, Lauramine Oxide, Lauramidopropylamine Oxide, Sodium Chloride, Fragrance, PEG-120 Methyl Glucose Dioleate, Cocamide MEA, Citric Acid, Sodium Benzoate, Tetrasodium EDTA, Blue 1, Red 33

* Encountered in household settings

Questions? 1-800-258-DIAL (3425)

© 2014 & Distributed by THE DIAL CORPORATION
a Henkel COMPANY SCOTTSDALE, AZ 85255

Made in USA

The distinctive design and elements of this package are proprietary and
owned by The Dial Corporation, A Henkel Company

Patent Pending

DOSAGE AND ADMINISTRATION

Topical liquid

INDICATIONS AND USAGE

For handwashing to decrease bacteria on skin

PACKAGE LABEL

KILLS 99.9% OF GERMS*

New Active!

TOTAL CLEAN FORMULA

Refill ONLY with Dial® Total Clean Formula

Dial Lavender and Twilight Jasmine

Hand Soap with Moisturizer

Antibacterial

7.5 FL OZ (221 mL)